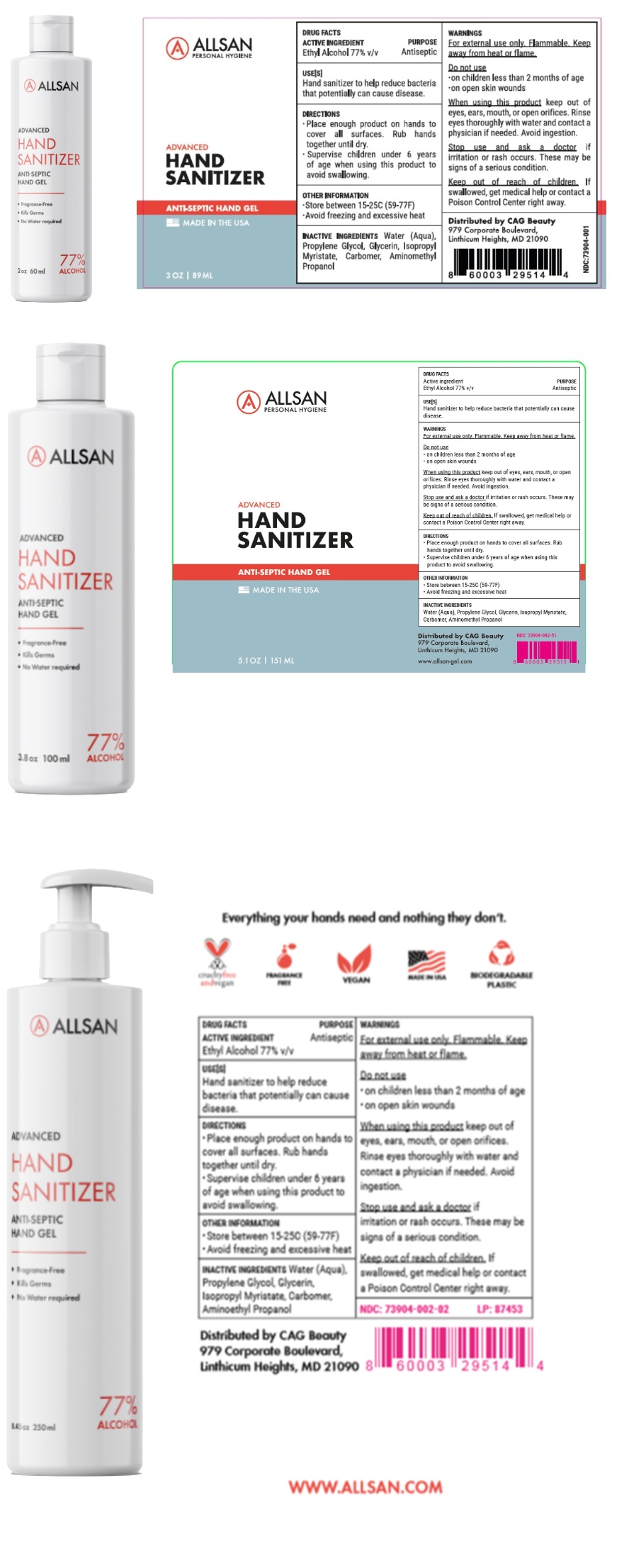 DRUG LABEL: ALLSAN ADVANCED HAND SANITIZER
NDC: 73904-002 | Form: GEL
Manufacturer: C-Care LLC
Category: otc | Type: HUMAN OTC DRUG LABEL
Date: 20200714

ACTIVE INGREDIENTS: ALCOHOL 77 mL/100 mL
INACTIVE INGREDIENTS: WATER; PROPYLENE GLYCOL; GLYCERIN; ISOPROPYL MYRISTATE; CARBOMER HOMOPOLYMER, UNSPECIFIED TYPE; AMINOMETHYLPROPANOL

ALLSAN ADVANCED HAND SANITIZER

ACTIVE INGREDIENT

Ethyl Alcohol 77% v/v

PURPOSE

Antiseptic

USE[S]

Hand sanitizer to help reduce bacteria that potentially can cause disease.

WARNINGS

For external use only. Flammable. Keep away from heat or flame.

Do not use

•on children less than 2 months of age

•on open skin wounds

When using this product keep out of eyes, ears, mouth, or open orifices. Rinse eyes thoroughly with water and contact a physician if needed. Avoid ingestion.

Stop use and ask a doctor if irritation or rash occurs. These may be signs of a serious condition.

Keep out of reach of children. If swallowed, get medical help or contact a Poison Control Center right away.

DIRECTIONS

• Place enough product on hands to cover all surfaces. Rub hands together until dry.

• Supervise children under 6 years of age when using this product to avoid swallowing.

OTHER INFORMATION

• Store between 15-25C (59-77F)

• Avoid freezing and excessive heat

INACTIVE INGREDIENTS

Water (Aqua), Propylene Glycol, Glycerin, Isopropyl Myristate, Carbomer, Aminomethyl Propanol

PERSONAL HYGIENE

ANTI-SEPTIC HAND GEL

MADE IN THE USA

Distributed by CAG Beauty

979 Corporate Boulevard,

Linthicum Heights, MD 21090